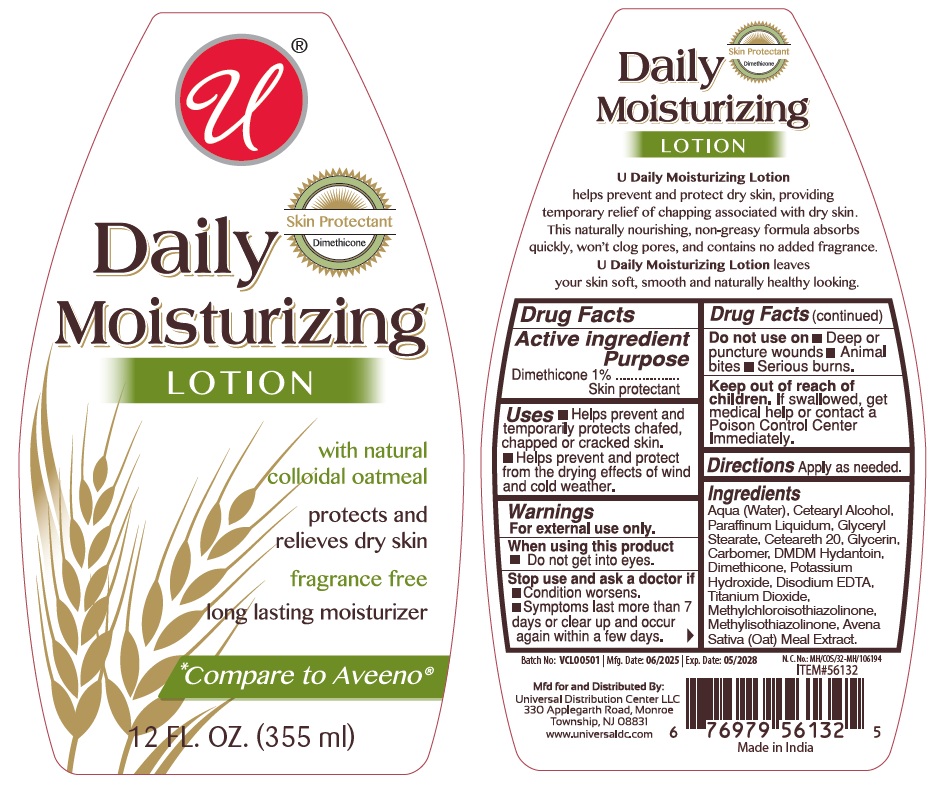 DRUG LABEL: Dimethicone 1 Skin Protectant
NDC: 52000-417 | Form: LOTION
Manufacturer: Universal Distribution Center LLC
Category: otc | Type: HUMAN OTC DRUG LABEL
Date: 20250724

ACTIVE INGREDIENTS: DIMETHICONE, UNSPECIFIED 1 g/100 mL
INACTIVE INGREDIENTS: WATER; CETOSTEARYL ALCOHOL; MINERAL OIL; GLYCERYL MONOSTEARATE; POLYOXYL 20 CETOSTEARYL ETHER; GLYCERIN; CARBOMER HOMOPOLYMER, UNSPECIFIED TYPE; DMDM HYDANTOIN; POTASSIUM HYDROXIDE; EDETATE DISODIUM; TITANIUM DIOXIDE; METHYLCHLOROISOTHIAZOLINONE; METHYLISOTHIAZOLINONE; OATMEAL

Daily Moisturizing LOTION

Active ingredient

Dimethicone 1%

Purpose

Skin protectant

Uses

• Helps prevent and temporarily protects chafed, chapped or cracked skin.
• Helps prevent and protect from the drying effects of wind and cold weather.

Warnings

For external use only.

When using this product
• Do not get into eyes.

Stop use and ask a doctor if
• Conditions worsens.
• Symptoms last more than 7 days or clear up and occur again within a few days.

Do not use on • Deep or puncture wounds • Animal bites • Serious burns.

Keep out of reach of children. If swallowed, get medical help or contact a Poison Control Center Immediately.

Directions

Apply as needed.

Ingredients

Aqua (Water), Cetearyl Alcohol, Paraffinum Liquidum, Glyceryl Stearate, Ceteareth 20, Glycerin, Carbomer, DMDM Hydantoin, Dimethicone, Potassium Hydroxide, Disodium EDTA, Titanium Dioxide, Methylchloroisothiazolinone, Methylisothiazolinone, Avena Sativa (Oat) Meal Extract.

with natural colloidal oatmeal

protects and relieves dry skin

fragrance free

long lasting moisturizer

*Compare to Aveeno®

U Daily Moisturizing Lotion helps prevent and protect dry skin, providing temporary relief of chapping associated with dry skin. This naturally nourishing, non-greasy formula absorbs quickly, won't clog pores, and contains no added fragrance.

U Daily Moisturizing Lotion leaves your skin soft, smooth and naturally healthy looking.

Mfd for and Distributed By:
Universal Distribution Center LLC
330 Applegarth Road, Monroe
Township, NJ 08831

www.universaldc.com

Made in India